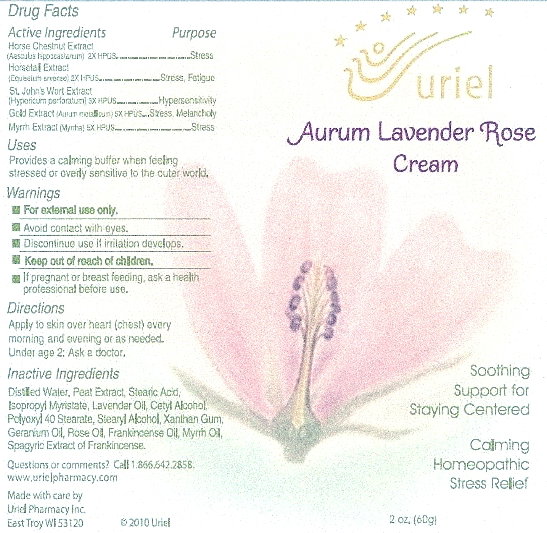 DRUG LABEL: Aurum Lavender Rose
NDC: 48951-1194 | Form: CREAM
Manufacturer: Uriel Pharmacy Inc
Category: homeopathic | Type: HUMAN OTC DRUG LABEL
Date: 20100412

ACTIVE INGREDIENTS: HORSE CHESTNUT 2 [hp_X]/1 1; EQUISETUM ARVENSE TOP 2 [hp_X]/1 1; HYPERICUM PERFORATUM 3 [hp_X]/1 1; GOLD 5 [hp_X]/1 1; MYRRH 5 [hp_X]/1 1
INACTIVE INGREDIENTS: WATER; STEARIC ACID; LAVENDER OIL; POLYOXYL 40 STEARATE; CETYL ALCOHOL; STEARYL ALCOHOL; XANTHAN GUM; PELARGONIUM GRAVEOLENS LEAF OIL; ROSE OIL; FRANKINCENSE

Aurum Lavender Rose Cream - 60 gm

Active Ingredients

Drug Facts

Active Ingredients Purpose
Horse Chestnut Extract
(Aesculus hippocastanum) 2X HPUS.....................................Stress
Horsetail Extract
(Equisetum arvense) 2X HPUS.................................Stress, Fatigue
St. John’s Wort Extract
(Hypericum perforatum) 3X HPUS...........................Hypersensitivity
Gold Extract (Aurum metallicum) 5X HPUS.........Stress, Melancholy
Myrrh Extract (Myrrha) 5X HPUS..........................................Stress

Purpose

Uses
Provides a calming buffer when feeling
stressed or overly sensitive to the outer world.

Warnings

For external use only.

When Using

Avoid contact with eyes.
Discontinue use if irritation develops.

Keep out of reach of children

Pregnancy or Breast Feeding section

If pregnant or breast-feeding, ask a health professional before use.

Dosage and Administration

Directions
Apply to skin over heart (chest) every morning and evening or as needed. Under age 2: Ask a doctor.

Inactive Ingredients

Distilled Water, Peat Extract, Stearic Acid, Isopropyl Myristate, Lavender Oil, Cetyl Alcohol, Polyoxyl 40 Stearate, Stearyl Alcohol, Xanthan Gum, Geranium Oil, Rose Oil, Frankincense Oil, Myrrh Oil, Spagyric Extract of Frankincense.

Questions section

Questions or comments? Call 1.866.642.2858
www.urielpharmacy.com
Made with care by
Uriel Pharmacy Inc.
East Troy, WI 53120 © 2010 Uriel

Principal Display Panel

Aurum Lavender Rose
Cream
Soothing
Support for
Staying Centered
Calming
Homeopathic
Stress Relief
2 oz.(60g)